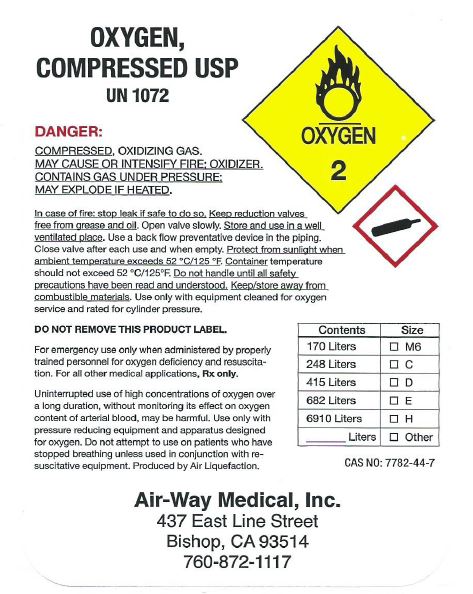 DRUG LABEL: Oxygen
NDC: 54483-0001 | Form: GAS
Manufacturer: Air-Way Medical, Inc.
Category: prescription | Type: HUMAN PRESCRIPTION DRUG LABEL
Date: 20190107

ACTIVE INGREDIENTS: OXYGEN 99 L/100 L

Oxygen